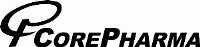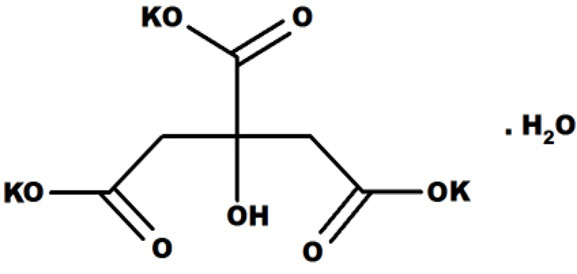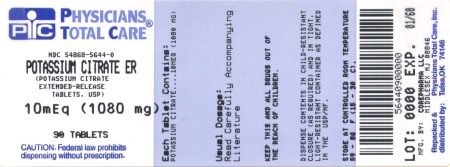 DRUG LABEL: Potassium Citrate
NDC: 54868-5644 | Form: TABLET, EXTENDED RELEASE
Manufacturer: Physicians Total Care, Inc.
Category: prescription | Type: HUMAN PRESCRIPTION DRUG LABEL
Date: 20100218

ACTIVE INGREDIENTS: POTASSIUM CITRATE 1080 mg/1 1
INACTIVE INGREDIENTS: CARNAUBA WAX; MAGNESIUM STEARATE; STEARIC ACID

POTASSIUM CITRATE EXTENDED-RELEASE TABLETS USP
5 mEq (540 mg) and 10 mEq (1080 mg)
Rx only

DESCRIPTION

Potassium citrate USP is a citrate salt of potassium and has the chemical name 1,2,3-Propanetricarboxylic acid, 2-hydroxy-, tripotassium salt, monohydrate. Its molecular formula is K3C6H 5O7.H2O , and its structural formula is: M.W. 324.41

Potassium citrate USP is a white granular powder that is soluble in water at 154 g/100 ml, almost insoluble in alcohol, and insoluble in organic solvents.

Potassium citrate extended-release tablets USP are supplied as wax matrix tablets, containing 5 mEq (540 mg) potassium citrate or 10 mEq (1080 mg) potassium citrate, for oral administration. In addition, potassium citrate extended-release tablets USP contain the inactive ingredients carnauba wax, magnesium stearate and stearic acid.

CLINICAL PHARMACOLOGY

When potassium citrate is given orally, the metabolism of absorbed citrate produces an alkaline load. The induced alkaline load in turn increases urinary pH and raises urinary citrate by augmenting citrate clearance without measurably altering ultrafilterable serum citrate. Thus, potassium citrate therapy appears to increase urinary citrate principally by modifying the renal handling of citrate, rather than by increasing the filtered load of citrate. The increased filtered load of citrate may play some role, however, as in small comparisons of oral citrate and oral bicarbonate, citrate had a greater effect on urinary citrate.

In addition to raising urinary pH and citrate, potassium citrate increases urinary potassium by approximately the amount contained in the medication. In some patients, potassium citrate causes a transient reduction in urinary calcium.

The changes induced by potassium citrate produce a urine that is less conducive to the crystallization of stone-forming salts (calcium oxalate, calcium phosphate and uric acid). Increased citrate in the urine, by complexing with calcium, decreases calcium ion activity and thus the saturation of calcium oxalate. Citrate also inhibits the spontaneous nucleation of calcium oxalate and calcium phosphate (brushite).

The increase in urinary pH also decreases calcium ion activity by increasing calcium complexation to dissociated anions. The rise in urinary pH also increases the ionization of uric acid to more soluble urate ion.

Potassium citrate therapy does not alter the urinary saturation of calcium phosphate, since the effect of increased citrate complexation of calcium is opposed by the rise in pH-dependent dissociation of phosphate. Calcium phosphate stones are more stable in alkaline urine.

In the setting of normal renal function, the rise in urinary citrate following a single dose begins by the first hour and lasts for 12 hours. With multiple doses the rise in citrate excretion reaches its peak by the third day and averts the normally wide circadian fluctuation in urinary citrate, thus maintaining urinary citrate at a higher, more constant level throughout the day. When the treatment is withdrawn, urinary citrate begins to decline toward the pre-treatment level on the first day.

The rise in citrate excretion is directly dependent on the potassium citrate dosage. Following long-term treatment, potassium citrate at a dosage of 60 mEq/day raises urinary citrate by approximately 400 mg/day and increases urinary pH by approximately 0.7 units.

In patients with severe renal tubular acidosis or chronic diarrheal syndrome where urinary citrate may be very low (<100 mg/day), potassium citrate may be relatively ineffective in raising urinary citrate. A higher dose of potassium citrate may therefore be required to produce a satisfactory citraturic response. In patients with renal tubular acidosis in whom urinary pH may be high, potassium citrate produces a relatively small rise in urinary pH.

INDICATIONS AND USAGE

Potassium citrate extended-release tablets are indicated for the management of renal tubular acidosis (RTA) with calcium stones, hypocitraturic calcium oxalate nephrolithiasis of any etiology, and uric acid lithiasis with or without calcium stones.

CONTRAINDICATIONS

Potassium citrate extended-release tablets are contraindicated in patients with hyperkalemia (or who have conditions predisposing them to hyperkalemia), as a further rise in serum potassium concentration may produce cardiac arrest. Such conditions include: chronic renal failure, uncontrolled diabetes mellitus, acute dehydration, strenuous physical exercise in unconditioned individuals, adrenal insufficiency, extensive tissue breakdown, or the administration of a potassium-sparing agent (such as triamterene, spironolactone or amiloride).

Potassium citrate extended-release tablets are contraindicated in patients in whom there is cause for arrest or delay in tablet passage through the gastrointestinal tract, such as those suffering from delayed gastric emptying, esophageal compression, intestinal obstruction or stricture or those taking anticholinergic medication. Because of its ulcerogenic potential, potassium citrate extended-release tablets should not be given to patients with peptic ulcer disease.

Potassium citrate extended-release tablets are contraindicated in patients with active urinary tract infection (with either urea-splitting or other organisms, in association with either calcium or struvite stones). The ability of potassium citrate extended-release tablets to increase urinary citrate may be attenuated by bacterial enzymatic degradation of citrate. Moreover, the rise in urinary pH resulting from potassium citrate therapy might promote further bacterial growth.

Potassium citrate extended-release tablets are contraindicated in patients with renal insufficiency (glomerular filtration rate of less than 0.7 ml/kg/min), because of the danger of soft tissue calcification and increased risk for the development of hyperkalemia.

WARNINGS

HYPERKALEMIA: In patients with impaired mechanisms for excreting potassium, potassium citrate administration can produce hyperkalemia and cardiac arrest. Potentially fatal hyperkalemia can develop rapidly and be asymptomatic. The use of potassium citrate in patients with chronic renal failure, or any other condition which impairs potassium excretion such as severe myocardial damage or heart failure, should be avoided.

INTERACTION WITH POTASSIUM-SPARING DIURETICS
Concomitant administration of potassium citrate and a potassium-sparing diuretic (such as triamterene, spironolactone or amiloride) should be avoided, since the simultaneous administration of these agents can produce severe hyperkalemia.

GASTROINTESTINAL LESIONS
Because of reports of upper gastrointestinal mucosal lesions following administration of potassium chloride (wax-matrix), and endoscopic examination of the upper gastrointestinal mucosa was performed in 30 normal volunteers after they had taken glycopyrrolate 2 mg. p.o. t.i.d., potassium citrate 95 mEq/day, wax-matrix potassium chloride 96 mEq/day or wax matrix placebo, in thrice daily schedule in the fasting state for one week. Potassium citrate and the wax-matrix formulation of potassium chloride were indistinguishable but both were significantly more irritating than the wax-matrix placebo. In a subsequent similar study, lesions were less severe when glycopyrrolate was omitted.

Solid dosage forms of potassium chloride have produced stenotic and/or ulcerative lesions of the small bowel and deaths. These lesions are caused by a high local concentration of potassium ions in the region of the dissolving tablets, which injured the bowel. In addition, perhaps because wax-matrix preparations are not enteric-coated and release some of their potassium content in the stomach, there have been reports of upper gastrointestinal bleeding associated with these products. The frequency of gastrointestinal lesions with wax-matrix potassium chloride products is estimated at one per 100,000 patient-years. Experience with potassium citrate is limited, but a similar frequency of gastrointestinal lesions should be anticipated.

If there is severe vomiting, abdominal pain or gastro-intestinal bleeding, potassium citrate should be discontinued immediately and the possibility of bowel perforation or obstruction investigated.

PRECAUTIONS

Information For Patients:
Physicians should consider reminding the patient of the following:

- To take each dose without crushing, chewing or sucking the tablet.
- To take this medicine only as directed. This is especially important if the patient is also taking both diuretics and digitalis preparations.
- To check with physician if there is trouble swallowing tablets or if the tablet seems to stick in the throat.
- To check with the doctor at once if tarry stools or other evidence of gastrointestinal bleeding is noticed.

Laboratory Tests:Regular serum potassium determinations are recommended. Careful attention should be paid to acid-base balance, other serum electrolyte levels, the electrocardiogram, and the clinical status of the patient, particularly in the presence of cardiac disease, renal disease or acidosis.

Drug Interactions:POTASSIUM-SPARING DIURETICS: SeeWARNINGS section.

DRUGS THAT SLOW GASTROINTESTINAL TRANSIT TIME (such as anticholinergics) can be expected to increase the gastrointestinal irritation produced by potassium salts. (see CONTRAINDICATIONS section).

Carcinogenesis, Mutagenesis, Impairment of Fertility: Long-term carcinogenicity studies in animals have not been performed.

Pregnancy Category C:Animal reproduction studies have not been conducted with potassium citrate. It is also not known whether potassium citrate can cause fetal harm when administered to a pregnant woman or can affect reproduction capacity. Potassium citrate should be given to a pregnant woman only if clearly needed.

Nursing Mothers:The normal potassium ion content of human milk is about 13 mEq/l. It is not known if potassium citrate has an effect on this content. Caution should be exercised when potassium citrate is administered to a nursing woman.

Pediatric Use: Safety and effectiveness in children have not been established.

ADVERSE REACTIONS

Some patients may develop minor gastrointestinal complaints during potassium citrate therapy, such as abdominal discomfort, vomiting, diarrhea, loose bowel movements or nausea. These symptoms are due to the irritation of the gastrointestinal tract, and may be alleviated by taking the dose with meals or snack, or by reducing the dosage. Patients may find intact matrices in feces. (see also CONTRAINDICATIONS,WARNINGS

OVERDOSAGE

The administration of potassium salts to persons without predisposing conditions for hyperkalemia (see CONTRAINDICATIONS) rarely causes serious hyperkalemia at recommended dosages. It is important to recognize that hyperkalemia is usually asymptomatic and may be manifested only by an increased serum potassium concentration and characteristic electrocardiographic changes (peaking of T-wave, loss of P-wave, depression of S-T segment and prolongation of the QT interval). Late manifestations include muscle paralysis and cardiovascular collapse from cardiac arrest.

Treatment measures for hyperkalemia include the following: (1) elimination of potassium-rich foods, medications containing potassium, and of potassium-sparing diuretics, (2) intravenous administration of 300-500 ml/hr of 10% dextrose solution containing 10-20 units of insulin/1000 ml, (3) correction of acidosis, if present, with intravenous sodium bicarbonate, and (4) use of exchange resins, hemodialysis or peritoneal dialysis.

In treating hyperkalemia, it should be recalled that in patients who have been stabilized on digitalis, too rapid a lowering of the serum potassium concentration can produce digitalis toxicity.

DOSAGE AND ADMINISTRATION

Treatment with potassium citrate extended-release tablets should be added to a regimen that limits salt intake (avoidance of foods with high salt content and of added salt at the table) and encourages high fluid intake (urine volume should be at least two liters per day). The objective of treatment with potassium citrate extended-release tablets is to provide potassium citrate in sufficient dosage to restore normal urinary citrate (greater than 320 mg/day and as close to the normal mean of 640 mg/day as possible), and to increase urinary pH to a level of 6.0 to 7.0.

In patients with severe hypocitraturia (urinary citrate of less than 150 mg/day), therapy should be initiated at a dosage of 60 mEq/day (20 mEq three times/day or 15 mEq four times/day with meals or within 30 minutes after meals or bedtime snack). In patients with mild-moderate hypocitraturia (>150 mg/day), potassium citrate extended-release tablets should be initiated at a dosage of 30 mEq/day (10 mEq three times/day with meals). Twenty-four hour urinary citrate and/or urinary pH measurements should be used to determine the adequacy of the initial dosage and to evaluate the effectiveness of any dosage change. In addition, urinary citrate and/or pH should be measured every four months.

Doses of potassium citrate extended-release tablets greater than 100 mEq/day have not been studied and should be avoided.

Serum electrolytes (sodium, potassium, chloride and carbon dioxide), serum creatinine, and complete blood count should be monitored every four months. Treatment should be discontinued if there is hyperkalemia, a significant rise in serum creatinine, or a significant fall in blood hematocrit or hemoglobin.

HOW SUPPLIED

Potassium citrate extended-release tablets USP 10 mEq (1080 mg) are pale yellow, capsule shaped compressed tablets debossed cor 149 on one side and other side is plain. They are supplied as follows:

Bottles of 30 (NDC 54868-5644-1)

Bottles of 90 (NDC 54868-5644-0)

Store at 20°C to 25°C (68°F to 77°F).excursions permitted to 15 to 30°C(59 to 86°F) [see USP Controlled Room Temperature].

Store in a tight container as defined in the USP.

Keep this and all drugs out of the reach of children.

Manufactured by:
Corepharma LLC
Middlesex, NJ 08846

Distributed by:
Rising Pharmaceuticals,Inc
Allendale,NJ 07401

MF # 718
May 2009

Relabeling and Repackaging by:
Physicians Total Care, Inc.
Tulsa, OK 74146

PRINCIPAL DISPLAY PANEL

Potassium citrate extended-release tablets USP 10 mEq (1080 mg)